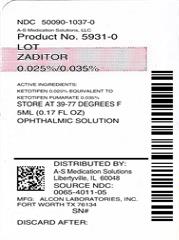 DRUG LABEL: Zaditor 
NDC: 50090-1037 | Form: SOLUTION
Manufacturer: A-S Medication Solutions
Category: otc | Type: HUMAN OTC DRUG LABEL
Date: 20171109

ACTIVE INGREDIENTS: KETOTIFEN FUMARATE .35 mg/1 mL
INACTIVE INGREDIENTS: Benzalkonium Chloride; Glycerin; Sodium Hydroxide; Hydrochloric Acid; Water

DRUG FACTS

OTC - ACTIVE INGREDIENT SECTION

Ketotifen (0.025%)
(equivalent to ketotifen fumarate 0.035%)

OTC - PURPOSE SECTION

Antihistamine

INDICATIONS & USAGE SECTION

Temporarily relieves itchy eyes due to pollen, ragweed, grass, animal hair and dander.

WARNINGS SECTION

For external use only

Do Not Use

- if solution changes color or becomes cloudy
- if you are sensitive to any ingredient in this product
- to treat contact lens related irritation

WHEN USING THIS PRODUCT

- do not touch tip of container to any surface to avoid contamination
- remove contact lenses before use
- wait at least 10 minutes before reinserting contact lenses after use
- replace cap after each use

STOP USE AND ASK A DOCTOR IF YOU EXPERIENCE ANY OF THE FOLLOWING

- eye pain
- changes in vision
- redness of the eye
- itching worsens or lasts for more than 72 hours

OTC - KEEP OUT OF REACH OF CHILDREN SECTION

If swallowed, get medical help or contact a Poison Control Center right away.

DOSAGE & ADMINISTRATION SECTION

- Adults and children 3 years of age and older: Put 1 drop in the affected eye(s) twice daily, every 8-12 hours, no more than twice per day.
- Children under 3 years of age: Consult a doctor

OTHER INFORMATION

- Only for use in the eye.
- Store between 4°-25°C (39°-77°F).

INACTIVE INGREDIENT SECTION

benzalkonium chloride 0.01%, glycerol, purified water, sodium hydroxide and/or hydrochloric acid

HOW SUPPLIED

Product: 50090-1037

NDC: 50090-1037-0 5 mL in a BOTTLE, DROPPER

QUESTIONS?

call toll-free
1-800-757-9195
MedInfo@AlconLabs.com
www.zaditor.com
Serious side effects associated with use of this product may be reported to this number.